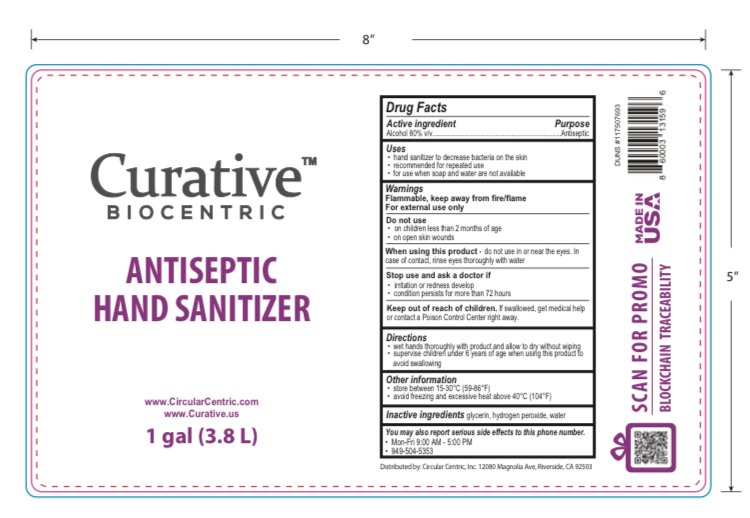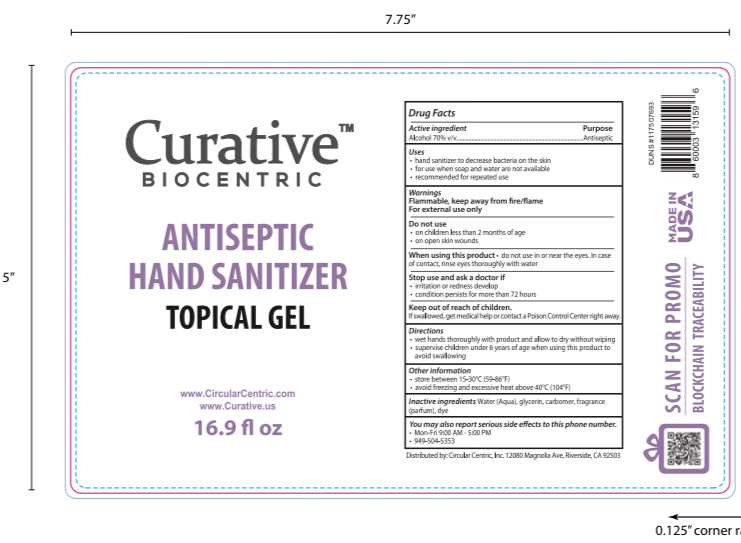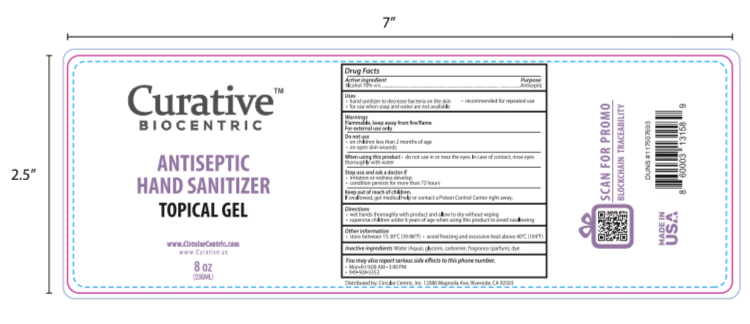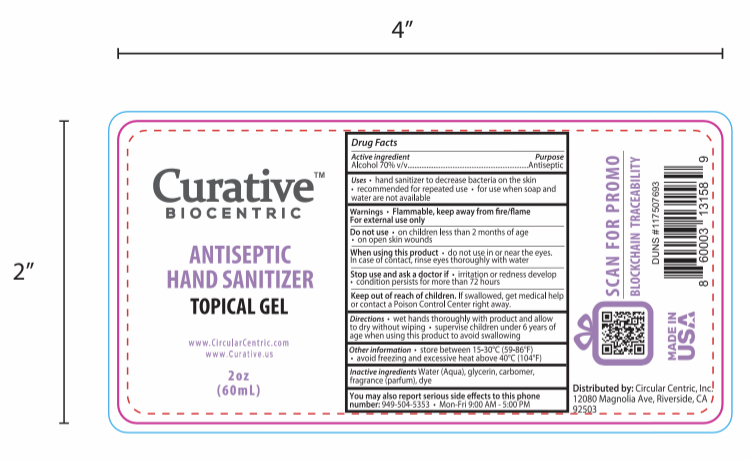 DRUG LABEL: Curative Biocentric Antiseptic Hand Sanitizer
NDC: 77094-444 | Form: GEL
Manufacturer: Circular Centric, Inc.
Category: otc | Type: HUMAN OTC DRUG LABEL
Date: 20200724

ACTIVE INGREDIENTS: ALCOHOL 70 mL/100 mL
INACTIVE INGREDIENTS: FD&C BLUE NO. 1 0.00001 mL/100 mL; GLYCERIN 2 mL/100 mL; CARBOMER 940 0.25 mL/100 mL; WATER; D&C RED NO. 33 0.00001 mL/100 mL

Curative Biocentric Antiseptic Hand Sanitizer

This is a hand sanitizer manufactured according to the Temporary Policy for Preparation of Certain Alcohol-Based Hand Sanitizer Products During the Public Health Emergency (CoViD-19); Guidance for Industry.

The hand sanitizer is manufactured using only the following United States Pharmacopoeia (USP) grade ingredients in the preparation of the product (percentage in final product formulation):

Alcohol (ethanol) (USP or Food Chemical Codex (FCC) grade) (80%, volume/volume (v/v)) in an aqueous solution denatured according to Alcohol and Tobacco Tax and Trade Bureau regulations in 27 CFR part 20.

1. Glycerol (2.00% v/v).
2. Carbomer Homopolymer Type C (0.25% v/v).
3. Sterile distilled water or boiled cold water
4. Fragrance Lavender (parfum)
5. FD&C Blue No. 1 and FD&C Red No. 33

The firm does not add other active or inactive ingredients than stated above. Different or additional ingredients may impact the quality and potency of the product.

Active Ingredient(s)

Alcohol 70% v/v. Purpose: Antiseptic

Purpose

Antiseptic, Hand Sanitizer

Use

Hand Sanitizer to help reduce bacteria that potentially can cause disease. For use when soap and water are not available.

Warnings

For external use only. Flammable. Keep away from fire or flame

Do not use

- in children less than 2 months of age
- on open skin wounds

When using this product keep out of eyes, ears, and mouth. In case of contact with eyes, rinse eyes thoroughly with water.
Stop use and ask a doctor if irritation or rash occurs. These may be signs of a serious condition.
Keep out of reach of children. If swallowed, get medical help or contact a Poison Control Center right away.

Stop use and ask a doctor if irritation or rash occurs. These may be signs of a serious condition.

Keep out of reach of children. If swallowed, get medical help or contact a Poison Control Center right away.

Directions

- Place enough product on hands to cover all surfaces. Rub hands together until dry.
- Supervise children under 6 years of age when using this product to avoid swallowing.

Other information

- Store between 15-30C (59-86F)
- Avoid freezing and excessive heat above 40C (104F)

Inactive ingredients

glycerin, carbomer, fragrance (parfum), dye, purified water (aqua) USP

Package Label - Principal Display Panel

60 mL NDC: 77094-400-02

236 mL NDC: 77094-400-08

500 mL NDC: 77094-400-16

3785 mL NDC: 77094-400-01